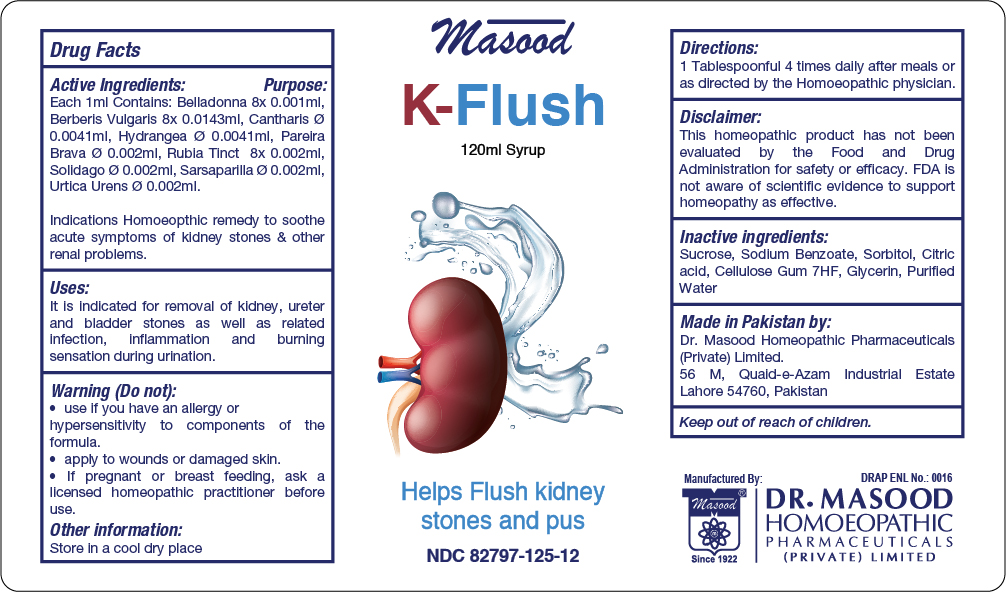 DRUG LABEL: K Flush
NDC: 82797-125 | Form: SYRUP
Manufacturer: Dr. Masood Homeopathic Pharmaceuticals Private Limited
Category: homeopathic | Type: HUMAN OTC DRUG LABEL
Date: 20240404

ACTIVE INGREDIENTS: BELLADONNA LEAF 0.12 mg/120 mL; HYDRANGEA ARBORESCENS BARK 0.492 mg/120 mL; URTICA URENS FLOWER 0.24 mg/120 mL; SARSAPARILLA 0.24 mg/120 mL; SOLIDAGO CANADENSIS FLOWERING TOP 0.24 mg/120 mL; BERBERIS VULGARIS FRUIT 1.7 mg/120 mL; LYTTA VESICATORIA 0.492 mg/120 mL; RUBIA CORDIFOLIA ROOT 0.24 mg/120 mL
INACTIVE INGREDIENTS: ANHYDROUS CITRIC ACID 0.06 mg/120 mL; SUCROSE 42 mg/120 mL; SODIUM BENZOATE 0.42 mg/120 mL; SORBITOL SOLUTION 70% 18 mL/120 mL; GLYCERIN 12 mL/120 mL; WATER 120 mL/120 mL; .ALPHA.-CELLULOSE 0.48 mg/120 mL

DOSAGE AND ADMINISTRATION

1 tablespoon full 4 times daily or as directed by homeopathic physician

Inactive ingredients:

Sucrose, Sodium Benzoate, Sorbitol, Citric acid, Cellulose Gum 7HF, Glycerin, Purified Water

INDICATIONS AND USAGE

It is indicated for removal of kidney, ureter and bladder stones as well as related infection, inflammation and burning sensation during urination.

ACTIVE INGREDIENT

Belladonna , Berberls Vulgaris, Cantharis , Hydrangea, Parelra Brava, Rubia Tinct, Solidago, Sarsaparilla, Urtica Urens

Keep out of reach of children.

Active Ingredients Purpose

Belladonna 8x Cystitis, burning pain in urinary tract. Acute Urinary Infections. Spasmodic pains along ureter

Berberls Vulgarls Used for Renal troubles

Cantharis Helps control frequency and urgency of urine

Hydrangea Renal colic

Parelra Brava Useful in renal colic, prostatic affection and catarrh of the bladder

Rubia Tinct Cures bladder stones

Solidago Renal coilic with dysuria

Sarsaparilla Renal colic

Urtica Urens Helps control urinary tact infection

Warnings:

Do not:

- use if you have an allergy or hypersensitivity to components of the formula
- use if pregnant or nursing

Stop use and ask a doctor if:

- condition worsens
- If symptoms persists for more than 7 days